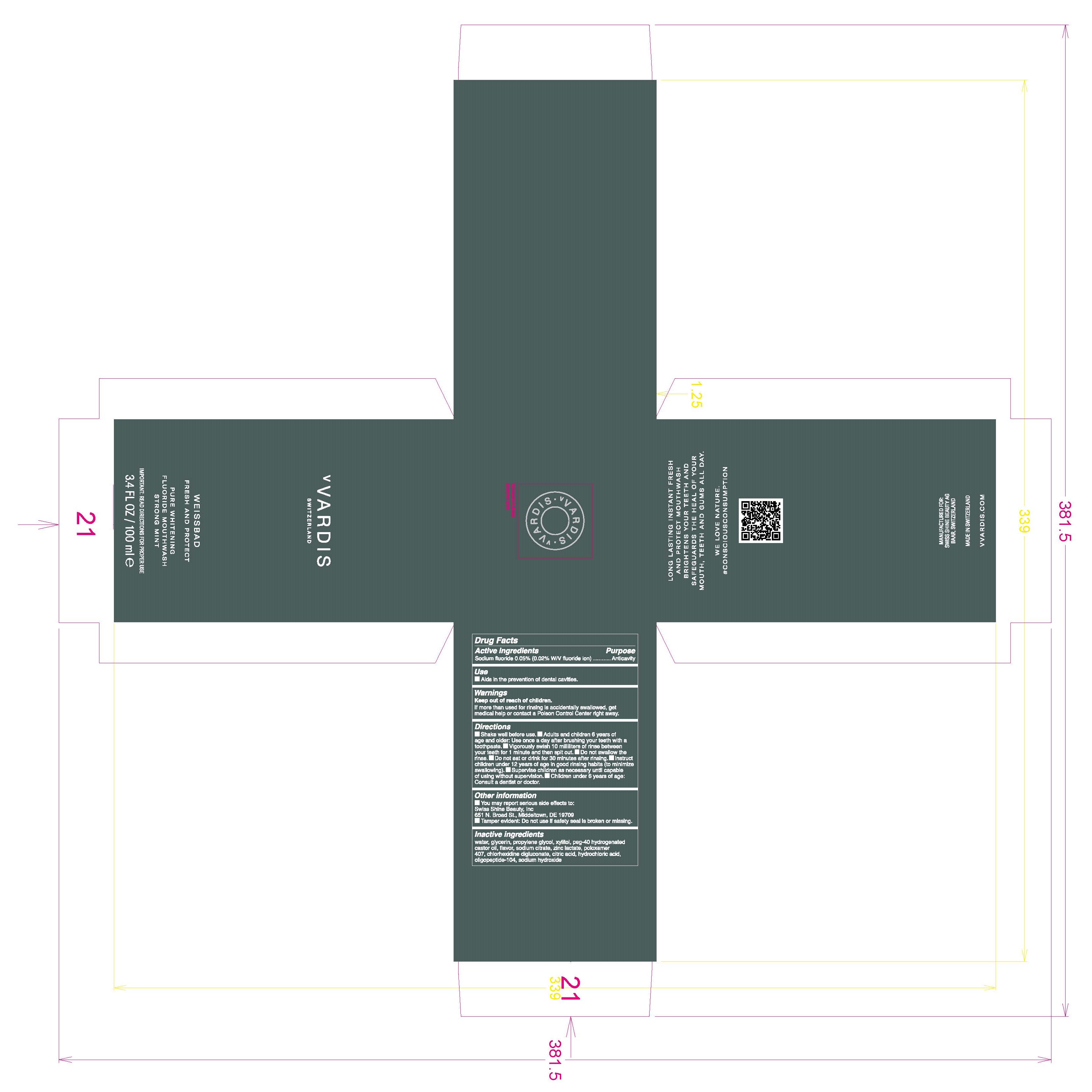 DRUG LABEL: Flouride Mouthwash Strong Mint
NDC: 79763-001 | Form: MOUTHWASH
Manufacturer: Swiss Shine Beauty AG
Category: otc | Type: HUMAN OTC DRUG LABEL
Date: 20200803

ACTIVE INGREDIENTS: SODIUM FLUORIDE 0.05 g/100 mL
INACTIVE INGREDIENTS: SODIUM CITRATE; CHLORHEXIDINE GLUCONATE; XYLITOL; POLOXAMER 407; HYDROCHLORIC ACID; SODIUM HYDROXIDE; GLYCERIN; ZINC LACTATE; WATER; CITRIC ACID MONOHYDRATE; PROPYLENE GLYCOL; POLYOXYL 40 HYDROGENATED CASTOR OIL

Flouride Mouthwash Strong Mint

Active Ingredients Purpose

Sodium Fluoride 0.05 (0.02% W/V fluoride ion) Anticavity

Use

- Aids in the prevention of dental cavities

Keep out of reach of children

if more than used for rinsing is accidenttally swallowed, get medical help or contact a Poison Control Center right away.

INDICATIONS AND USAGE

Do not swallow the rinse

Warnings

Keep out of reach of children

if more than used for rinsing is accidenttally swallowed, get medical help or contact a Poison Control Center right away.

Directions

- Shake well before use
- Adults and children 6 years of age and older: use once a day after brushing your teeth with a toothpaste.
- Vigorously swish 10 milliters of rinse between your teeth for 1 minute and then spit out.
- Do not eat or drink for 30 minutesafter rinsing.
- Instruct children under 12 year of age in good rinsing habits (to minimize swallowing).
- Supervise children as necessary until capable of using without supervision.
- Children under 6 years of age: consult a dentist or doctor.

Inactive ingredients

water, glycerin, propylene glycol, xylitol, peg-40 hydrogenated castor oil, flavor, sodium citrate,zinc lactate, poloxamer 407, chlorhexidine digluconate, citric acid, hydrochloric acid, oligopeptide-104, sodium hydroxide

PACKAGE LABEL

vVardis

Switzerland

WEISSBAD

FRESH AND PROTECT

PURE WHITENING

FLUORIDE MOUTHWASH

STRONG MINT

IMPORTANT: READ DIRECTIONS FOR PROPER USE

3.4 FL OZ / 100 ml